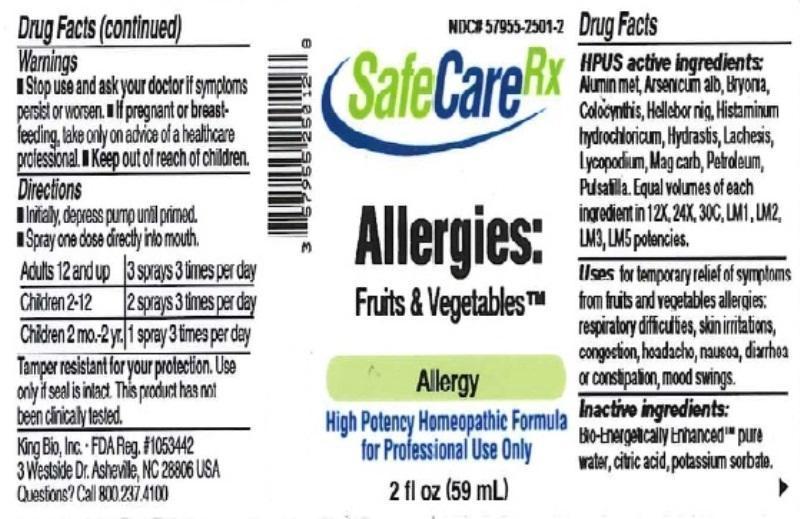 DRUG LABEL: Allergies Fruits and Vegetables
NDC: 57955-2501 | Form: LIQUID
Manufacturer: King Bio Inc.
Category: homeopathic | Type: HUMAN OTC DRUG LABEL
Date: 20150811

ACTIVE INGREDIENTS: ALUMINUM 12 [hp_X]/59 mL; ARSENIC TRIOXIDE 12 [hp_X]/59 mL; BRYONIA ALBA ROOT 12 [hp_X]/59 mL; CITRULLUS COLOCYNTHIS FRUIT PULP 12 [hp_X]/59 mL; HELLEBORUS NIGER ROOT 12 [hp_X]/59 mL; HISTAMINE DIHYDROCHLORIDE 12 [hp_X]/59 mL; GOLDENSEAL 12 [hp_X]/59 mL; LACHESIS MUTA VENOM 12 [hp_X]/59 mL; LYCOPODIUM CLAVATUM SPORE 12 [hp_X]/59 mL; MAGNESIUM CARBONATE 12 [hp_X]/59 mL; KEROSENE 12 [hp_X]/59 mL; PULSATILLA VULGARIS 12 [hp_X]/59 mL
INACTIVE INGREDIENTS: WATER; ANHYDROUS CITRIC ACID; POTASSIUM SORBATE

Allergies: Fruits and Vegetables

ACTIVE INGREDIENT

Drug Facts__________________________________________________________________________________________________________

HPUS active ingredients: Aluminium metallicum, Arsenicum album, Bryonia, Colocynthis, Helleborus niger, Histaminum hydrochloricum, Hydrastis canadensis, Lachesis mutus, Lycopodium clavatum, Magnesia carbonica, Petroleum, Pulsatilla. Equal volumes of each ingredient in 12X, 24X, 30C, LM1, LM2, LM3, LM5 potencies.

INDICATIONS AND USAGE

Uses for temporary relief of symptoms from fruits and vegetables allergies: respiratory difficulties, skin irritations, congestion, headacha, nausea, diarrhea or constipation, mood swings.

Inactive Ingredients:

Bio-Energetically Enhanced™ pure water, citric acid and potassium sorbate.

Warnings

- Stop use and ask your doctor if symptoms persist or worsen.
- If pregnant or breast-feeding, take only on advice of a healthcare professional.

- Keep out of reach of children.

Directions

- Initially, depress pump until primed.
- Spray one dose directly into mouth.
- Adults 12 and up: 3 sprays 3 times per day.
- Children 2-12: 2 sprays 3 times per day.
- Children 2 mo-2yr: 1 sprary 3 times per day.

OTHER SAFETY INFORMATION

Tamper resistant for your protection. Use only if seal is intact. This product has not been clinically tested.

PURPOSE

Uses for temporary relief of symptoms from fruits and vegetables allergies:

- respiratory difficulties
- skin irritations
- congestion
- headacha
- nausea
- diarrhea or constipation
- mood swings